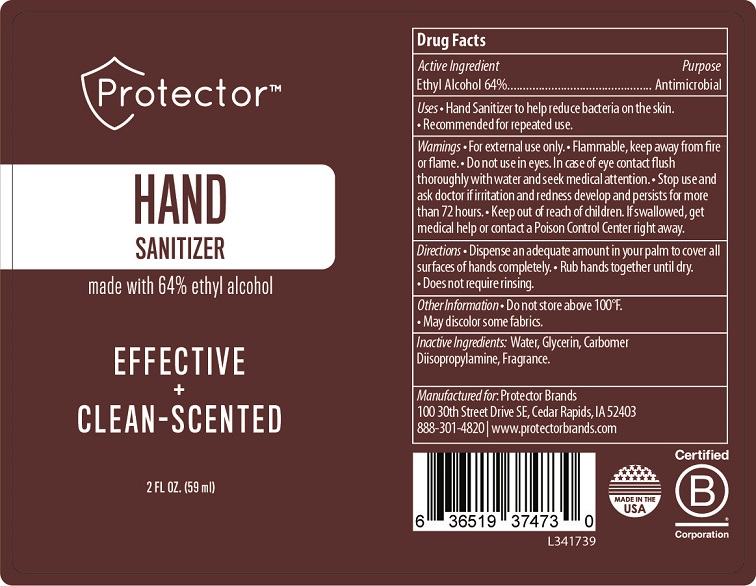 DRUG LABEL: Protector Brands Hand Sanitizer
NDC: 65692-2002 | Form: GEL
Manufacturer: Raining Rose, Inc.
Category: otc | Type: HUMAN OTC DRUG LABEL
Date: 20200413

ACTIVE INGREDIENTS: ALCOHOL 64 mL/100 mL
INACTIVE INGREDIENTS: WATER; GLYCERIN; CARBOMER HOMOPOLYMER, UNSPECIFIED TYPE; DIISOPROPYLAMINE

Protector Brands Hand Sanitizer

Drug Facts

Active Ingredient

Ethyl Alcohol 64%

Purpose

Antimicrobial

Uses
• Hand Sanitizer to help reduce bacteria on the skin.
• Recommended for repeated use.

WARNINGS

Warnings• For external use only. • Flammable, keep away from fire
or flame • Do not use in eyes. In case of eye contact flush
thoroughly with water and seek medical attention. • Stop use and
ask doctor if irritation and redness develop and persists for more
than 72 hours.

• Keep out of reach of children. If swallowed, get
medical help or contact a Poison Control Center right away.

Directions
• Dispense an adequate amount in your palm to cover all surfaces of hands completely.

• Rub hands together until dry. • Does not require rinsing.

Other Information
• Do not store above 100°F.
• May discolor some fabrics.

Inactive Ingredients: Water, Glycerin, Carbomer

Diisopropylamine, Fragrance.

Principal Display Package

ProtectorTM

HAND

SANITIZER

made with 64% ethyl alcohol

EFFECTIVE

+

CLEAN-SCENTED

2 FL OZ. (59 ml)

Manufactured for: Protector Brands

100 30th Street Drive SE, Cedar Rapids, IA 52403

888-301-4820| www.protectorbrands.com

L341739

res